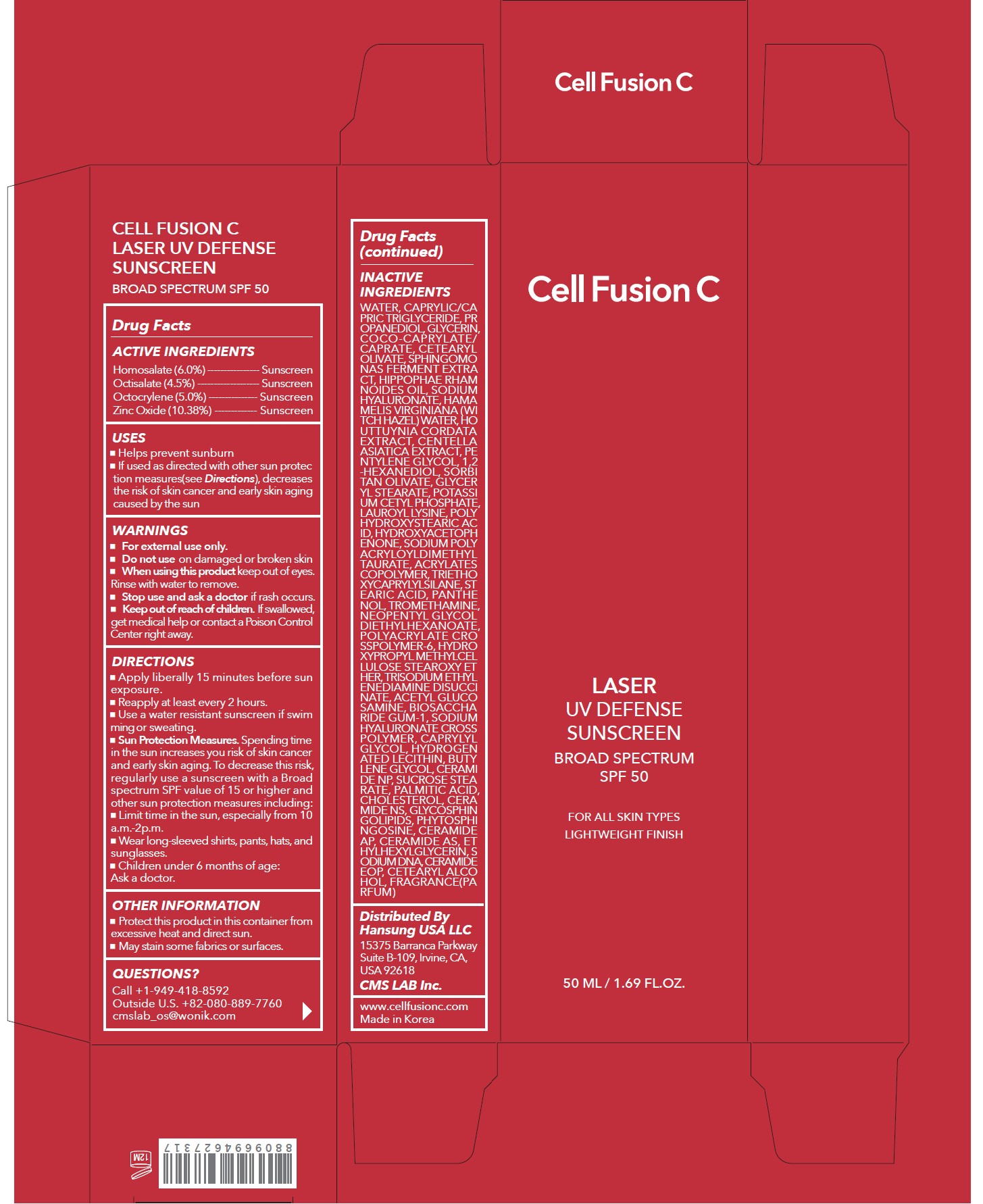 DRUG LABEL: Cell Fusion C Laser UV Defense Sunscreen Broad Spectrum SPF 50
NDC: 52554-9062 | Form: CREAM
Manufacturer: CMS LAB Inc.
Category: otc | Type: HUMAN OTC DRUG LABEL
Date: 20250214

ACTIVE INGREDIENTS: HOMOSALATE 6 g/50 mL; OCTOCRYLENE 5 g/50 mL; OCTISALATE 4.5 g/50 mL; ZINC OXIDE 10.38 g/50 mL
INACTIVE INGREDIENTS: WATER

52554-9062-1 Cell Fusion C Laser UV Defense Sunscreen Broad Spectrum SPF 50 50mL

Drug Facts

ACTIVE INGREDIENTS

Homosalate 6.0%
Octisalate 4.5%
Octocrylene 5.0%
Zinc Oxide 10.38%

PURPOSE

Sunscreen

USES

- Helps prevent sunburn
- If used as directed with other sun protection measures (see Directions), decreases the risk of skin cancer and early skin aging caused by the sun

WARNINGS

For external use only

- Do not use on damaged or broken skin

- When using this product keep out of the eyes. Rinse with water to remove.

- Stop use and ask a doctor if rash occurs

- Keep out of reach of children. If swallowed, get medical help or contact a Poison Control Center right away.

DIRECTIONS

- Apply generously and evenly 15 minutes before sun exposure.
- Reapply at least every 2 hours.
- Use a water resistant sunscreen if swimming or sweating.
- Sun Protection Measures. Spending time in the sun increases your risk of skin cancer and early skin aging. To decrease this risk, regularly use a sunscreen with a Broad Spectrum SPF value of 15 or higher and other sun protection measures including:

- Limit time in the sun, especially from 10 a.m.-2 p.m.
- Wear long-sleeved shirts, pants, hats, and sunglasses
- Children under 6 months of age: Ask a doctor.

OTHER INFORMATION

- Protect this product in this container from excessive heat and direct sun.
- May stain some fabrics or surfaces.

INACTIVE INGREDIENTS

Water, Caprylic/Capric Triglyceride, Propanediol, Glycerin, Coco-Caprylate/Caprate, Cetearyl Olivate, Sphingomonas Ferment Extract, Hippophae Rhamnoides Oil, Sodium Hyaluronate, Hamamelis Virginiana (Witch Hazel) Water, Houttuynia Cordata Extract, Centella Asiatica Extract, Pentylene Glycol, 1,2-Hexanediol, Sorbitan Olivate, Glyceryl Stearate, Potassium Cetyl Phosphate, Lauroyl Lysine, Polyhydroxystearic Acid, Hydroxyacetophenone, Sodium Polyacryloyldimethyl Taurate, Acrylates Copolymer, Triethoxycaprylylsilane, Stearic Acid, Panthenol, Tromethamine, Neopentyl Glycol Diethylhexanoate, Polyacrylate Crosspolymer-6, Hydroxypropyl Methylcellulose Stearoxy Ether, Trisodium Ethylenediamine Disuccinate, Acetyl Glucosamine, Biosaccharide Gum-1, Sodium Hyaluronate Crosspolymer, Caprylyl Glycol, Hydrogenated Lecithin, Butylene Glycol, Ceramide NP, Sucrose Stearate, Palmitic Acid, Cholesterol, Ceramide NS, Glycosphingolipids, Phytosphingosine, Ceramide AP, Ceramide AS, Ethylhexylglycerin, Sodium DNA, Ceramide EOP, Cetearyl Alcohol, Fragrance (Parfum)

QUESTIONS?

Call +1-949-418-8592
Outside U.S. +82-080-889-7760
cmslab_os@wonik.com

Distributed By
Hansung USA LLC
15375 Barranca Parkway
Suite B-109, Irvine, CA USA 92618
CMS LAB Inc.
www.cellfusionc.com
Made in Korea

PRINCIPAL DISPLAY PANEL: 50 ML / 1.69 FL.OZ. Carton

Cell Fusion C

LASER
UV DEFENSE
SUNSCREEN
BROAD SPECTRUM
SPF 50
FOR ALL SKIN TYPES
LIGHTWEIGHT FINISH
50 ML / 1.69 FL.OZ.